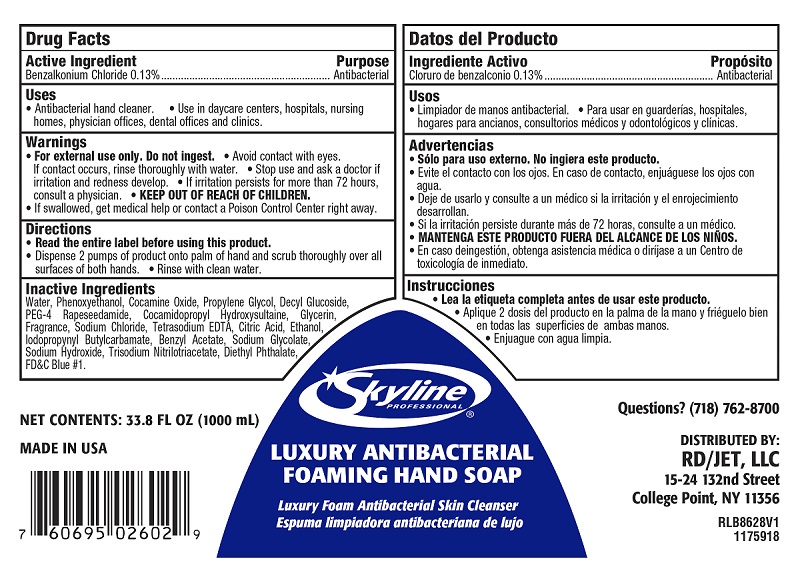 DRUG LABEL: RD Food Service DBA Restaurant Depot
NDC: 56131-711 | Form: SOAP
Manufacturer: RD Food Service DBA Restaurant Depot
Category: otc | Type: HUMAN OTC DRUG LABEL
Date: 20200731

ACTIVE INGREDIENTS: BENZALKONIUM CHLORIDE 0.13 1/1 mL
INACTIVE INGREDIENTS: WATER; N-ALKYL DIMETHYL BENZYL AMMONIUM CHLORIDE (C12-C18); COCAMINE OXIDE; PROPYLENE GLYCOL; MAGNESIUM NITRATE; PEG-4 RAPESEEDAMIDE; COCAMIDOPROPYL HYDROXYSULTAINE; GLYCERIN; SODIUM CHLORIDE; EDETATE SODIUM; 2-METHYLUNDECANAL; ALCOHOL; BENZYL ACETATE; SODIUM GLYCOLATE; SODIUM HYDROXIDE; TRISODIUM NITRILOTRIACETATE; FD&C BLUE NO. 1; ANHYDROUS CITRIC ACID; GERANIOL; METHYL DIHYDROJASMONATE (SYNTHETIC); METHYLCHLOROISOTHIAZOLINONE; METHYLISOTHIAZOLINONE; CITRAL; FORMALDEHYDE; CAPRYLYL/CAPRYL OLIGOGLUCOSIDE; LINALOOL, (+/-)-; LIME OIL; CITRONELLYL ACETATE; .BETA.-CITRONELLOL, (+/-)-; 2,4-DIMETHYL-3-CYCLOHEXENE CARBOXALDEHYDE; ALLYL CYCLOHEXANEPROPIONATE; GERANYL ACETATE

Luxury Antibacterial Foaming Hand Soap

Luxury Antibacterial Foaming Soap Active Ingredient

Benzalkonium Chloride 0.13%

Luxury Antibacterial Foaming Soap Purpose

Antibacterial

Luxury Antibacterial Foaming Soap Warnings

- For external use only. Do not ingest.
- Avoid contact with eyes. If contact occurs, rinse thoroughly with water.
- Stop use and ask a doctor if irritation and redness develop.
- If irritation persists for more than 72 hours, consult a physician.
- KEEP OUT OF REACH OF CHILDREN.
- If swallowed, get medical help or contact a Poison Control Center right away.

Luxury Antibacterial Foaming Soap Directions

- ?Read the entire label before using this product.
- ?Dispense 2 pumps of product onto palm of hand and scrub thoroughly over all surfaces of both hands.
- Rinse with clean water.

Luxury Antibacterial Foaming Soap Inactive Ingredients

Water, Phenoxyethanol, Cocamine Oxide, Propylene Glycol, Decyl Glucoside, PEG-4 Rapeseedamide, Cocamidopropyl Hydroxysultaine, Glycerin, Fragrance, Sodium Chloride, Tetrasodium EDTA, Citric Acid, Ethanol, Iodopropynyl Butylcarbamate, Benzyl Acetate, Sodium Glycolate, Sodium Hydroxide, Trisodium Nitrilotriacetate, Diethyl Phthalate, FD&C Blue #1.

Luxury Antibacterial Foaming Soap Questions

Questions? 888-GO BETCO (888-462-3826)

Luxury Antibacterial Foaming Soap Purpose

Purpose

Antibacterial

Luxury Antibacterial Foaming Soap Keep out of Reach of Children

KEEP OUT OF REACH OF CHILDREN

Luxury Antibacterial Foaming Soap

RD_759